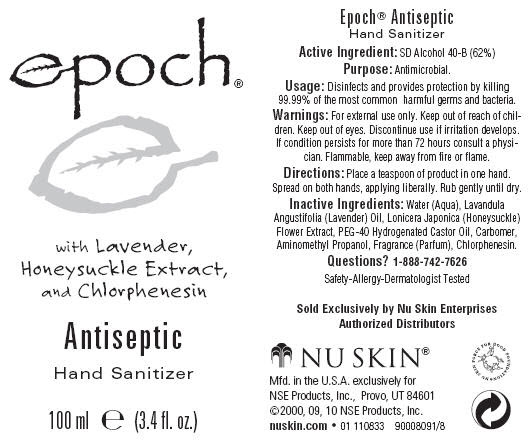 DRUG LABEL: Epoch 
NDC: 62839-1083 | Form: GEL
Manufacturer: NSE Products, Inc.
Category: otc | Type: HUMAN OTC DRUG LABEL
Date: 20220112

ACTIVE INGREDIENTS: Alcohol 61.9937 mL/100 mL
INACTIVE INGREDIENTS: WATER; LAVENDER OIL; LONICERA JAPONICA FLOWER; POLYOXYL 40 HYDROGENATED CASTOR OIL; AMINOMETHYLPROPANOL; CHLORPHENESIN

Epoch® Antiseptic Hand Sanitizer

Active Ingredient

SD Alcohol 40-B (62%)

Purpose

Antimicrobial.

Usage

Disinfects and provides protection by killing 99.99% of the most common harmful germs and bacteria.

Warnings

For external use only.

Keep out of reach of children.

WHEN USING

Keep out of eyes.

STOP USE

Discontinue use if irritation develops. If condition persists for more than 72 hours consult a physician.

WHEN USING

Flammable, keep away from fire or flame.

Directions

Place a teaspoon of product in one hand. Spread on both hands, applying liberally. Rub gently until dry.

Inactive Ingredients:

Water (Aqua), Lavandula Angustifolia (Lavender) Oil, Lonicera Japonica (Honeysuckle) Flower Extract, PEG-40 Hydrogenated Castor Oil, Carbomer, Aminomethyl Propanol, Fragrance (Parfum), Chlorphenesin.

Questions?

1-888-742-7626

Mfd. in the U.S.A. exclusively for
NSE Products, Inc., Provo, UT 84601

PRINCIPAL DISPLAY PANEL - 100 ml Bottle Label

epoch®

with Lavender,
Honeysuckle Extract,
and Chlorphenesin

Antiseptic

Hand Sanitizer

100 ml e (3.4 fl. oz.)